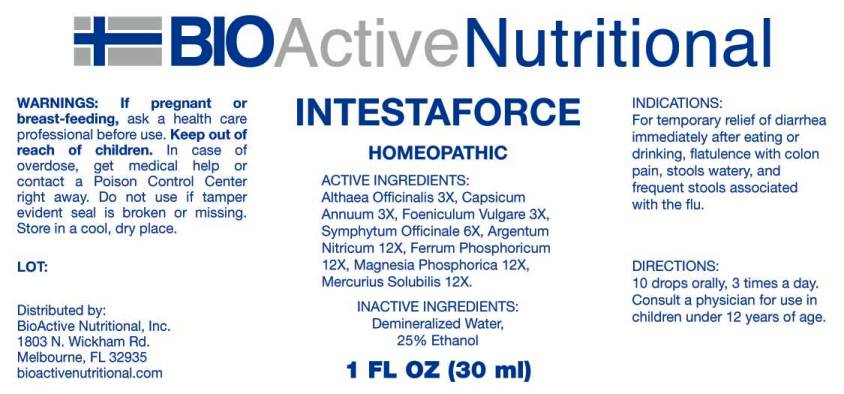 DRUG LABEL: Intestaforce
NDC: 43857-0407 | Form: LIQUID
Manufacturer: BioActive Nutritional, Inc.
Category: homeopathic | Type: HUMAN OTC DRUG LABEL
Date: 20160811

ACTIVE INGREDIENTS: ALTHAEA OFFICINALIS ROOT 3 [hp_X]/1 mL; CAPSICUM 3 [hp_X]/1 mL; FENNEL SEED 3 [hp_X]/1 mL; COMFREY ROOT 6 [hp_X]/1 mL; SILVER NITRATE 12 [hp_X]/1 mL; FERRUM PHOSPHORICUM 12 [hp_X]/1 mL; MAGNESIUM PHOSPHATE, DIBASIC TRIHYDRATE 12 [hp_X]/1 mL; MERCURIUS SOLUBILIS 12 [hp_X]/1 mL
INACTIVE INGREDIENTS: WATER; ALCOHOL

Drug Facts:

ACTIVE INGREDIENTS:

Althaea Officinalis 3X, Capsicum Annuum 3X, Foeniculum Vulgare 3X, Symphytum Officinale 6X, Argentum Nitricum 12X, Ferrum Phosphoricum 12X, Magnesia Phosphorica 12X, Mercurius Solubilis 12X.

INDICATIONS:

For temporary relief of diarrhea immediately after eating or drinking, flatulence with colon pain, stools watery, and frequent stools associated with the flu.

WARNINGS:

If pregnant or breast-feeding, ask a health care professional before use.

Keep out of reach of children. In case of overdose, get medical help or contact a Poison Control Center right away.

Do not use if tamper evident seal is broken or missing.

Store in cool, dry place.

Keep out of reach of children. In case of overdose, get medical help or contact a Poison Control Center right away.

DIRECTIONS:

10 drops orally, 3 times a day. Consult a physician for use in children under 12 years of age.

INDICATIONS:

For temporary relief of diarrhea immediately after eating or drinking, flatulence with colon pain, stools watery, and frequent stools associated with the flu.

INACTIVE INGREDIENTS:

Demineralized Water, 25% Ethanol

QUESTIONS:

Distributed by:
BioActive Nutritional, Inc.
1803 N. Wickham Rd.
Melbourne, FL 32935
bioactivenutritional.com

PACKAGE LABEL DISPLAY:

BIOActive Nutritional

INTESTAFORCE

HOMEOPATHIC

1 FL OZ (30 ml)